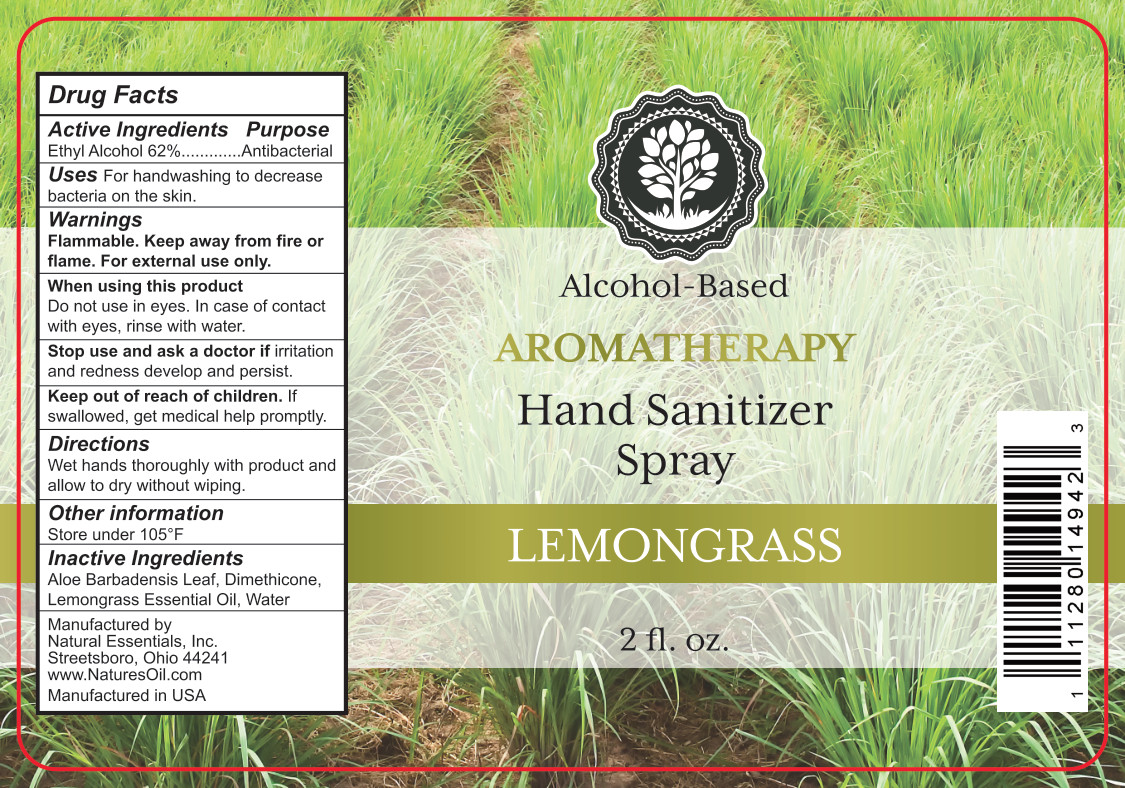 DRUG LABEL: Lemongrass Hand Sanitizer
NDC: 66902-547 | Form: SPRAY
Manufacturer: Natural Essentials, Inc.
Category: otc | Type: HUMAN OTC DRUG LABEL
Date: 20241031

ACTIVE INGREDIENTS: ALCOHOL 0.62 mL/1 mL
INACTIVE INGREDIENTS: ALOE VERA LEAF; WATER; DIMETHICONE; LEMONGRASS OIL

Active Ingredients

Ethyl Alcohol 62%

Purpose

Antibacterial

Uses

For handwashing to decrease bacteria on the skin.

Warnings

Flammable. Keep away from fire of flame. For external use only.

When using this product

Do not use in eyes. In case of contact with eyes, rinse with water.

Stop use and ask a doctor if

irritation and redness develop and persist.

Keep out of reach of children

If swallowed, get medical help promptly.

Directions

Wet hands thoroughly with product and allow to dry without wiping.

Other information

Store under 105°F

Inactive Ingredients

Aloe Barbadensis Leaf, Dimethicone, Lemongrass Essential Oil, Water

PACKAGE LABEL

Alcohol-Based

Aromatherapy

Hand Sanitizer Spray

Lemongrass

2 fl. oz